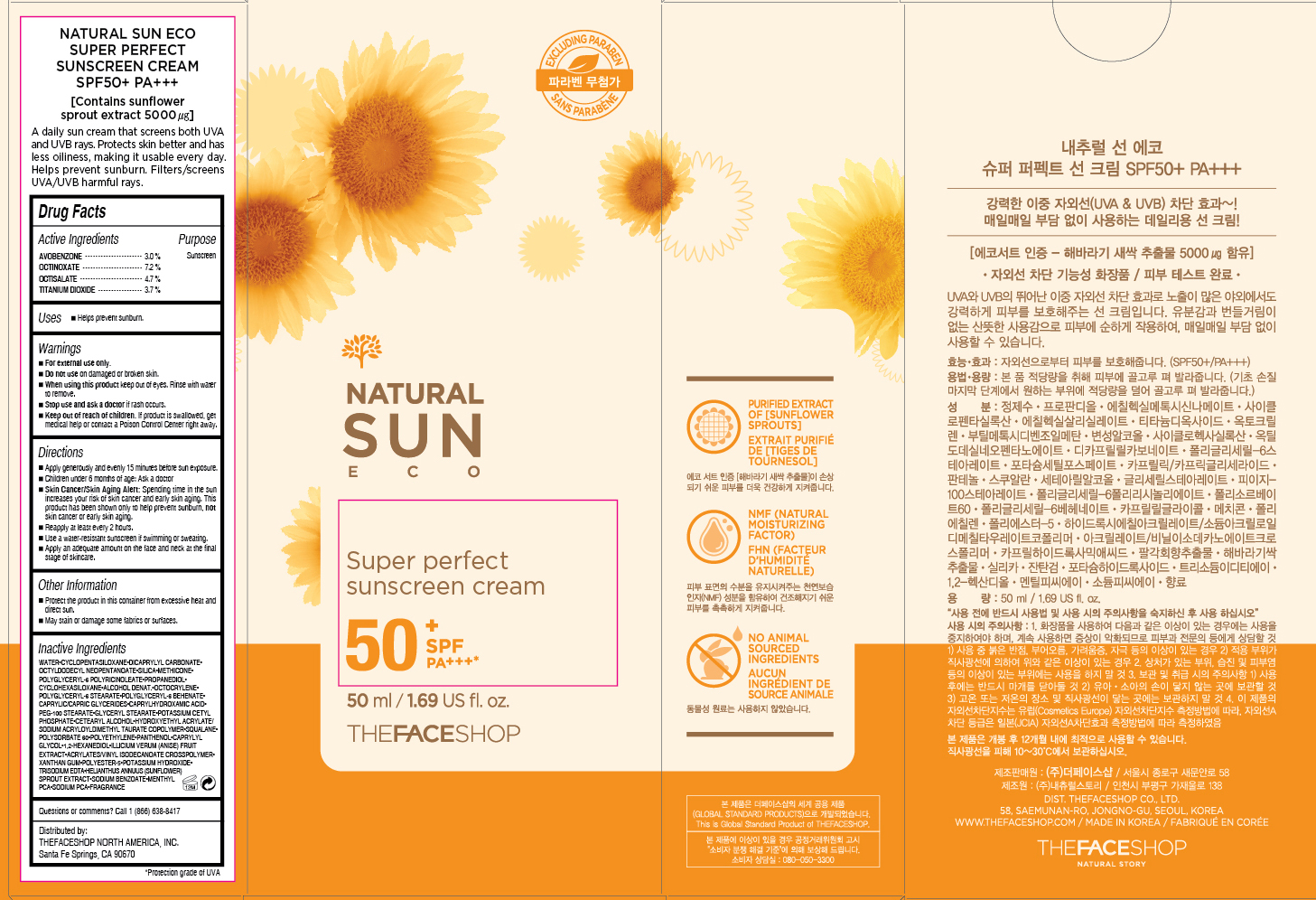 DRUG LABEL: NATURAL SUN ECO
NDC: 51523-173 | Form: CREAM
Manufacturer: THEFACESHOP CO., LTD.
Category: otc | Type: HUMAN OTC DRUG LABEL
Date: 20150929

ACTIVE INGREDIENTS: OCTINOXATE 3.6 g/50 mL; TITANIUM DIOXIDE 1.85 g/50 mL; OCTISALATE 2.35 g/50 mL; AVOBENZONE 1.5 g/50 mL
INACTIVE INGREDIENTS: WATER

NATURAL SUN ECO SUPER PERFECT SUNSCREEN CREAM SPF50+ PA+++ 31500173

Active Ingredients

Avobenzone 3.0 %
Octinoxate 7.2 %
Octisalate 4.7%
Titanium Dioxide 3.7%

Purpose

Sunscreen
Sunscreen
Sunscreen
Sunscreen

Uses

Helps prevent sunburn.

Warnings

For external use only.

Do not use on damaged or broken skin

When using this product keep out of eyes. Rinse with water to remove.

Stop use and ask a doctor if rash occurs.

Keep out of reach of children. If product is swallowed, get medical help or contact a Poison Control Center right away.

Directions

Apply generously and evenly 15 minutes before sun exposure.
Children under 6 months of age: Ask a doctor.
Skin Cancer/Skin Aging Alert: Spending time in the sun increases your risk of skin cancer and early skin aging. This product has been shown only to help prevent sunburn, not skin cancer or early skin aging.
Reapply at least every 2 hours.
Use a water-resistant sunscreen if swimming or sweating.

Apply an adequate amount on the face and neck at the final stage of skincare.

OTHER SAFETY INFORMATION

Protect the product in this container from excessive heat and direct sun.

May stain or damage some fabrics or surfaces.

Inactive Ingredients

WATER, CYCLOPENTASILOXANE, DICAPRYLYL CARBONATE, OCTYLDODECYL NEOPENTANOATE, SILICA, METHICONE, POLYGLYCERYL-6 POLYRICINOLEATE, PROPANEDIOL, CYCLOHEXASILOXANE, ALCOHOL DENAT., OCTOCRYLENE, POLYGLYCERYL-6 STEARATE, POLYGLYCERYL-6 BEHENATE, CAPRYLIC/CAPRIC GLYCERIDES, CAPRYLHYDROXAMIC ACID, PEG-100 STEARATE, GLYCERYL STEARATE, POTASSIUM CETYL PHOSPHATE, CETEARYL ALCOHOL, HYDROXYETHYL ACRYLATE/SODIUM ACRYLOYLDIMETHYL TAURATE COPOLYMER, SQUALANE, POLYSORBATE 60, POLYETHYLENE, PANTHENOL, CAPRYLYL GLYCOL, 1,2-HEXANEDIOL, ILLICIUM VERUM (ANISE) FRUIT EXTRACT, ACRYLATES/VINYL ISODECANOATE CROSSPOLYMER, XANTHAN GUM, POLYESTER-5, POTASSIUM HYDROXIDE, TRISODIUM EDTA, HELIANTHUS ANNUUS (SUNFLOWER) SPROUT EXTRACT, SODIUM BENZOATE, MENTHYL PCA, SODIUM PCA, FRAGRANCE

Questions or comments? Call 1-866-638-8417

Distributed by:

THEFACESHOP NORTH AMERICA, INC.

Santa Fe Springs, CA 90670

PACKAGE LABEL

NATURAL SUN ECO

SUPER PERFECT SUNSCREEN CREAM

SPF 50+ PA+++

Contains sunflower sprout extract 5000 µg

A daily sun cream that screens both UVA and UVB rays.

Protects skin better and has less oiliness, making it usable every day.

Helps prevent sunburn.

Filters/screens UVA/UVB harmful rays.